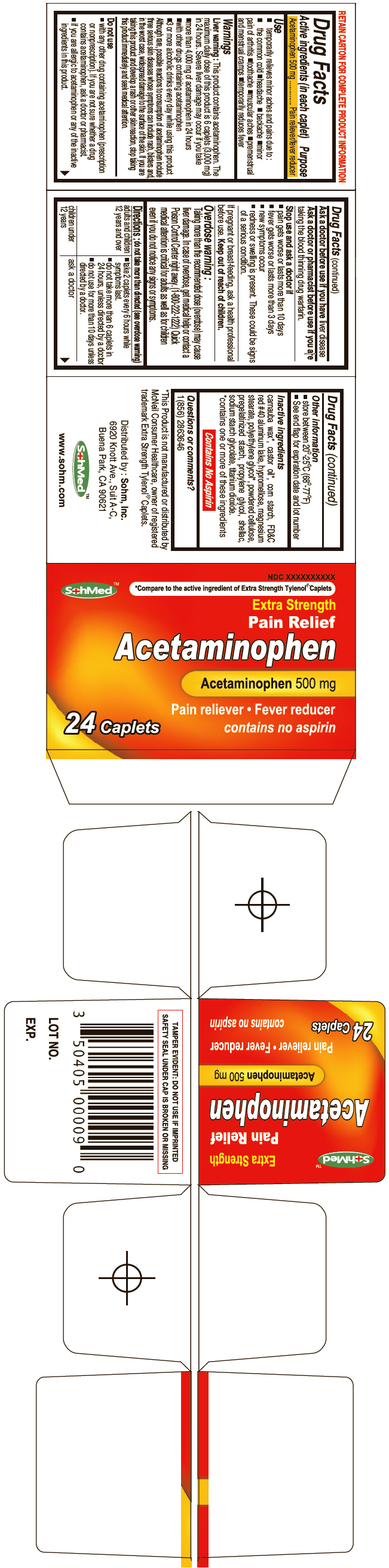 DRUG LABEL: SohMed Extra Strength
NDC: 50405-001 | Form: TABLET
Manufacturer: SOHM Inc.
Category: otc | Type: HUMAN OTC DRUG LABEL
Date: 20130819

ACTIVE INGREDIENTS: Acetaminophen 500 mg/1 1
INACTIVE INGREDIENTS: CARNAUBA WAX; CASTOR OIL; STARCH, CORN; FD&C Red No. 40; ALUMINUM OXIDE; HYPROMELLOSES; MAGNESIUM STEARATE; POLYETHYLENE GLYCOL 6000; POWDERED CELLULOSE; PROPYLENE GLYCOL; SHELLAC; SODIUM STARCH GLYCOLATE TYPE A CORN; TITANIUM DIOXIDE

SohMed™ Extra Strength

Drug Facts

Active ingredients (in each caplet)

Acetaminophen 500 mg

Purpose

Pain reliever/fever reducer

Use

- temporarily relieves minor aches and pains due to :
  - the common cold
  - headache
  - backache
  - minor pain of arthritis
  - toothache
  - muscular aches
  - premenstrual and menstrual cramps
- temporarily reduces fever

Warnings

Liver warning

This product contains acetaminophen. The maximum daily dose of this product is 6 caplets (3,000 mg) in 24 hours. Severe liver damage may occur if you take

- more than 4,000 mg of acetaminophen in 24 hours
- with other drugs containing acetaminophen
- 3 or more alcoholic drinks every day while using this product

Although rare, possible reactions to consumption of acetaminophen include three serious skin diseases whose symptoms can include rash, blisters and, in the worst case, widespread damage to the surface of the skin. If you are taking this product and develop a rash or other skin reaction, stop taking this product immediately and seek medical attention.

Do not use

- with any other drug containing acetaminophen (prescription or nonprescription). If you are not sure whether a drug contains acetaminophen, ask a doctor or pharmacist.
- if you are allergic to acetaminophen or any of the inactive ingredients in this product.

Ask a doctor before use if you have liver disease

Ask a doctor or pharmacist before use if you are taking the blood thinning drug warfarin.

Stop use and ask a doctor if

- pain gets worse or lasts more than 10 days
- fever gets worse or lasts more than 3 days
- new symptoms occur
- redness or swelling is present. These could be signs of a serious condition.

PREGNANCY OR BREAST FEEDING

If pregnant or breast-feeding, ask a health professional before use.

Keep out of reach of children.

Overdose warning

Taking more than the recommended dose (overdose) may cause liver damage. In case of overdose, get medical help or contact a Poison Control Center right away. (1-800-222-1222) Quick medical attention is critical for adults as well as for children even if you do not notice any signs or symptoms.

Directions

do not take more than directed (see overdose warning)

adults and children 12 years and over | - take 2 caplets every 6 hours while symptoms last. - do not take more than 6 caplets in 24 hours, unless directed by a doctor - do not use for more than 10 days unless directed by a doctor.
children under 12 years | ask a doctor

Other information

- store between 20°-25°C (68°-77°F)
- See end flap for expiration date and lot number

Inactive ingredients

carnauba wax [*contains one or more of these ingredients] , castor oil, corn starch, FD&C red #40 aluminum lake, hypromellose, magnesium stearate, polyethylene glycol, powdered cellulose, pregelatinized starch, propylene glycol, shellac, sodium starch glycolate, titanium dioxide.

Contains No Aspirin

Questions or comments?

1(856) 2863646

Distributed by : Sohm, Inc.
6920 Knott Ave., Suit A-C,
Buena Park, CA 90621

PRINCIPAL DISPLAY PANEL - 24 Tablet Bottle Carton

NDC XXXXXXXXXX

SohMed™

*Compare to the active ingredient of Extra Strength Tylenol® Caplets

Extra Strength

Pain Relief

Acetaminophen

Acetaminophen 500 mg

Pain reliever • Fever reducer

contains no aspirin

24 Caplets